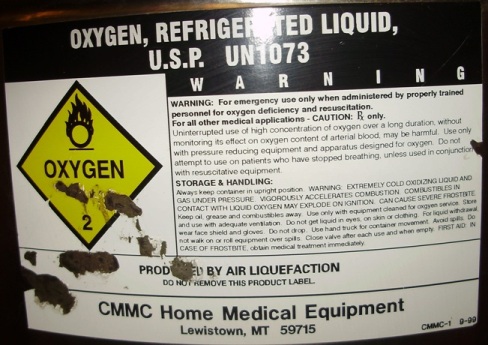 DRUG LABEL: Oxygen
NDC: 65567-001 | Form: GAS
Manufacturer: Central Montana Medical Facilities, Inc.
Category: prescription | Type: HUMAN PRESCRIPTION DRUG LABEL
Date: 20171221

ACTIVE INGREDIENTS: OXYGEN 990 mL/1 L

oxygen

PACKAGE LABEL

OXYGEN, REFRIGERATED LIQUID USP UN1073 OXYGEN 2
WARNING: For emergency use only when administered by properly trained personnel for oxygen deficiency and resuscitation. For all other medical applications, Rx Only.
Uninterrupted use of high concentration of oxygen over a long duration, without monitoring its effect on oxygen content of arterial blood, may be harmful. Use only with pressure reducing equipment and apparatus designed for oxygen. Do not attempt to use on patients who have stopped breathing, unless used in conjucation with resuscitative equipment.
STORAGE AND HANDLING:
Always keep container in upright position. WARNING: EXTREMELY COLD, OXIDIZING LIQUID AND GAS UNDER PRESSURE. VIGOROUSLY ACCELERATES COMBUSTION. COMBUSTIBLES IN CONTACT WITH LIQUID OXYGEN MAY EXPLODE ON IGNITION OR IMPACT. CAN CAUSE SEVERE FROSTBITE.
Keep oil, grease, and combustibles away. Use with equipment cleaned for oxygen service. Store and use with adequate ventilation. Do not get liquid in eyes, on skin, or clothing. For liquid withdrawal, wear face shield and gloves. Do not drop. Use hand truck for container movement. Avoid spills. Do not walk on or roll equipment over spills. Close valve after each use and when empty. FIRST AID IN CASE OF FROSTBITE, obtain medical treatment immediately.
PRODUCED BY AIR LIQUEFACTION.
DO NOT REMOVE THIS PRODUCT LABEL.
CMMC Home Medical Equipment
Lewistown, MT 59715